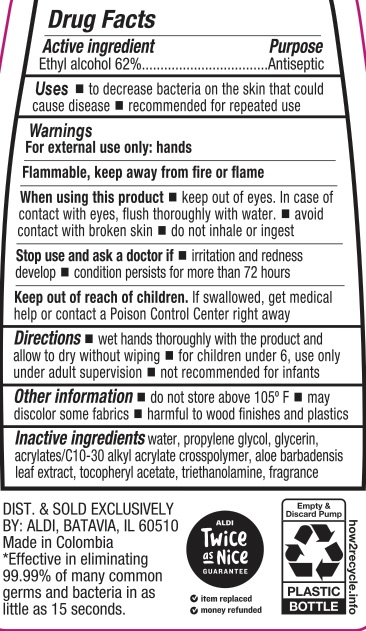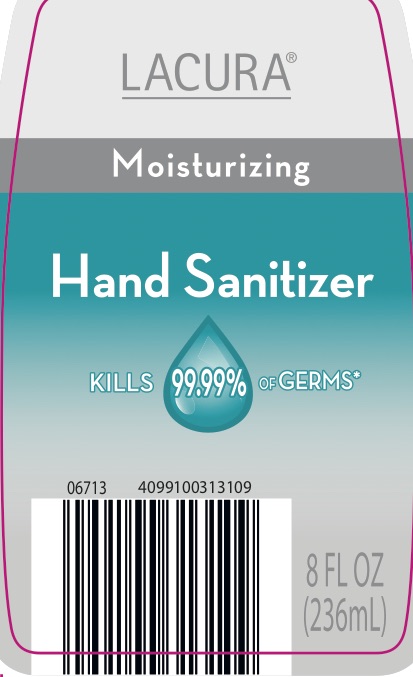 DRUG LABEL: Lacura Moisturizing Hand Sanitizer
NDC: 64024-008 | Form: LIQUID
Manufacturer: Aldi
Category: otc | Type: HUMAN OTC DRUG LABEL
Date: 20250613

ACTIVE INGREDIENTS: ALCOHOL 62 g/100 mL
INACTIVE INGREDIENTS: WATER; CARBOMER INTERPOLYMER TYPE A (ALLYL SUCROSE CROSSLINKED); GLYCERIN; PROPYLENE GLYCOL; TROLAMINE; .ALPHA.-TOCOPHEROL ACETATE; ALOE VERA LEAF

ACTIVE INGREDIENT

Ethyl Alcohol 62%

PURPOSE

Antiseptic

INDICATIONS AND USAGE

To decrease bacteria on the skin that could cause disease. Recommended for repeated use.

WARNINGS

For external use only: hands. Flammable, keep away from fire or flame. When using this product keep out of eyes. In case of contact with eyes, flush thoroughly with water. avoid contact with broken skin, do not inhale or ingest. Stop use and ask a doctor if irritation and redness develop, condition persists for more than 72 hours.

KEEP OUT OF REACH OF CHILDREN

If swallowed, get medical help or contact a Poison Control Center right away.

DOSAGE AND ADMINISTRATION

Wet hand thoroughly with the product and allow to dry without wiping. For children under 6, use only under adult supervision. Not recommended for infants.

INACTIVE INGREDIENT

Water, Propylene Glycol, Glycerin, Acrylates/C10-30 Alkyl Acrylate Crosspolymer, Aloe Barbadensis Leaf Extract, Tocopheryl Acetate, Triethanolamine, Fragrance.